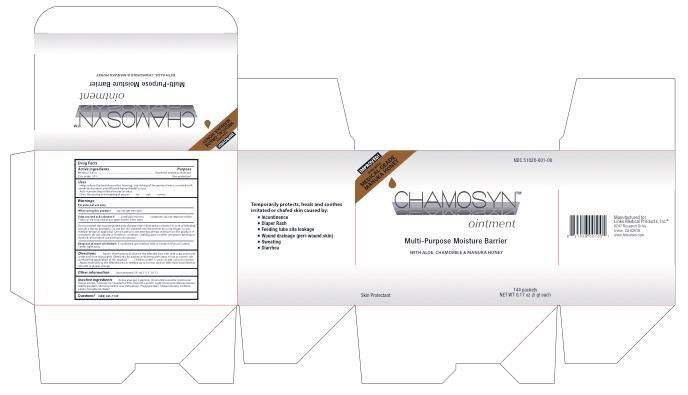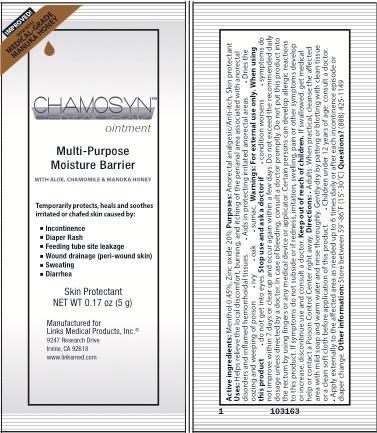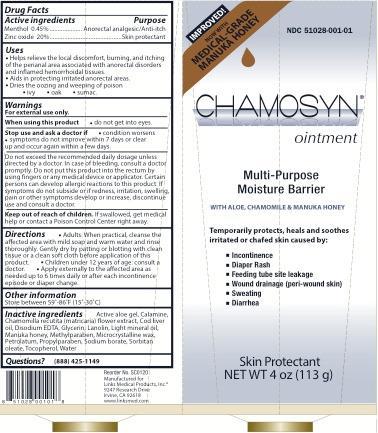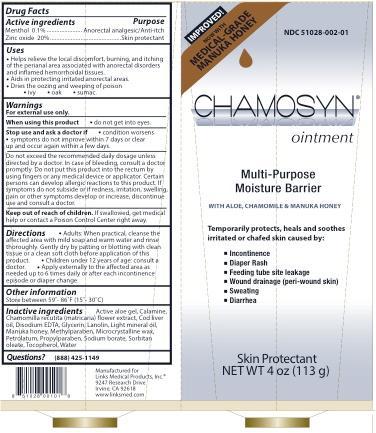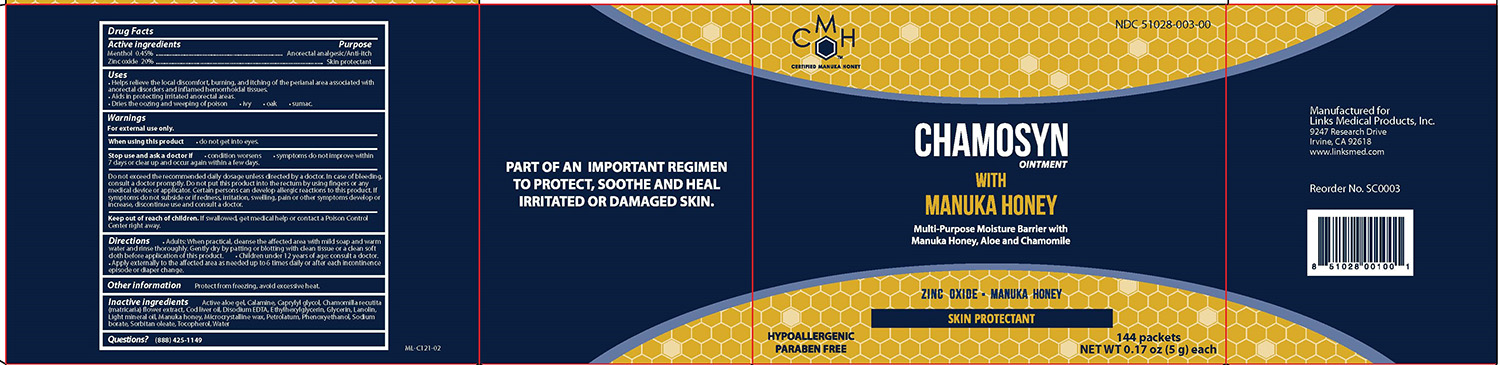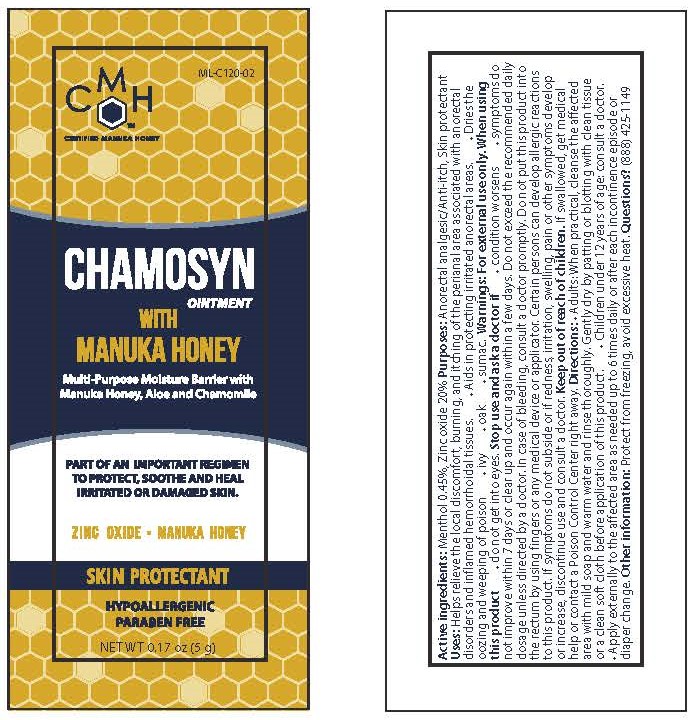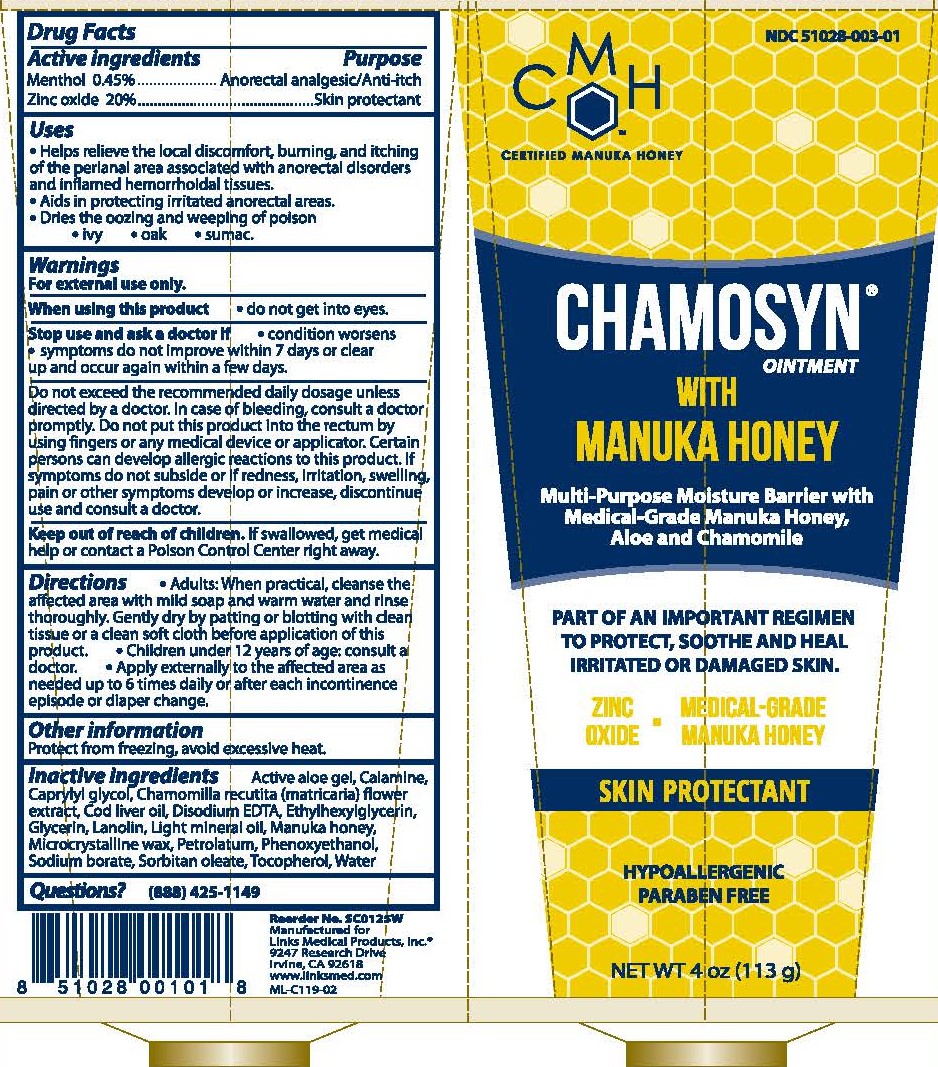 DRUG LABEL: Chamosyn
NDC: 51028-003 | Form: OINTMENT
Manufacturer: Links Medical Products
Category: otc | Type: HUMAN OTC DRUG LABEL
Date: 20250508

ACTIVE INGREDIENTS: MENTHOL 4.5 mg/1 g; ZINC OXIDE 200 mg/1 g
INACTIVE INGREDIENTS: ALOE VERA LEAF; FERRIC OXIDE RED; CAPRYLYL GLYCOL; CHAMOMILE; COD LIVER OIL; EDETATE DISODIUM; ETHYLHEXYLGLYCERIN; GLYCERIN; LANOLIN; LIGHT MINERAL OIL; HONEY; MICROCRYSTALLINE WAX; PETROLATUM; PHENOXYETHANOL; SODIUM BORATE; SORBITAN MONOOLEATE; TOCOPHEROL; WATER

Chamosyn with Manuka Honey

Active ingredients

- Menthol 0.45% or 0.1%
- Zinc oxide 20%

Purpose

- Anorectal analgesic/Anti-itch
- Skin protectant

Uses

- Helps relieve the local discomfort, burning, and itching of the perianal area associated with anorectal disorders and inflamed hemorrhoidal tissues.

- Aids in protecting irritated anorectal areas.

- Dries the oozing and weeping of poison
  - ivy
  - oak
  - sumac

Warnings

For external use only.

When using this product

- do not get into eyes

Stop use and ask a doctor if

- condition worsens
- symptoms do not improve within 7 days or clear up and occur again within a few days.

Do not exceed the recommended daily dosage unless directed by a doctor. In case of bleeding, consult a doctor promptly. Do not put this product into the rectum by using fingers or any medical device or applicator. Certain persons can develop allergic reactions to this product. If symptoms do not subside or if redness, irritation, swelling, pain or other symptoms develop or increase, discontinue use and consult a doctor.

Keep out of reach of children. If swallowed, get medical help or contact a Poison Control Center right away.

Directions

- Adults: When practical, cleanse the affected area with mild soap and warm water and rinse thoroughly. Gently dry by patting or blotting with clean tissue or a clean soft cloth before application of this product.
- Children under 12 years of age: consult a doctor.
- Apply externally to the affected area as needed up to 6 times daily or after each incontinence episode or diaper change.

Other information

Protect from freezing, avoid excessive heat.

Inactive Ingredients

Chamosyn

Active aloe gel, Calamine, Chamomilla recutita (matricaria) flower extract, Cod liver oil, Disodium EDTA, Glycerin, Lanolin, Light mineral oil, Manuka honey, Methylparaben, Microcrystalline wax, Petrolatum, Propylparaben, Sodium borate, Sorbitan oleate, Tocopherol, Water

Chamosyn - Paraben Free

Active aloe gel, Calamine, Caprylyl glycol, Chamomilla recutita (matricaria) flower extract, Cod liver oil, Disodium EDTA, Ethylhexylglycerin, Glycerin, Lanolin, Light mineral oil, Manuka honey, Microcrystalline wax, Petrolatum, Phenoxyethanol, Sodium borate, Sorbitan oleate, Tocopherol, Water

Questions?

(888) 425-1149

Chamosyn Ointment (0.45% Menthol)

Tube Label

Packet Labels

Chamosyn Ointment (0.45% Menthol) - Paraben Free

Tube Label

Packet Labels

Chamosyn Ointment (0.1% Menthol)

Tube Label